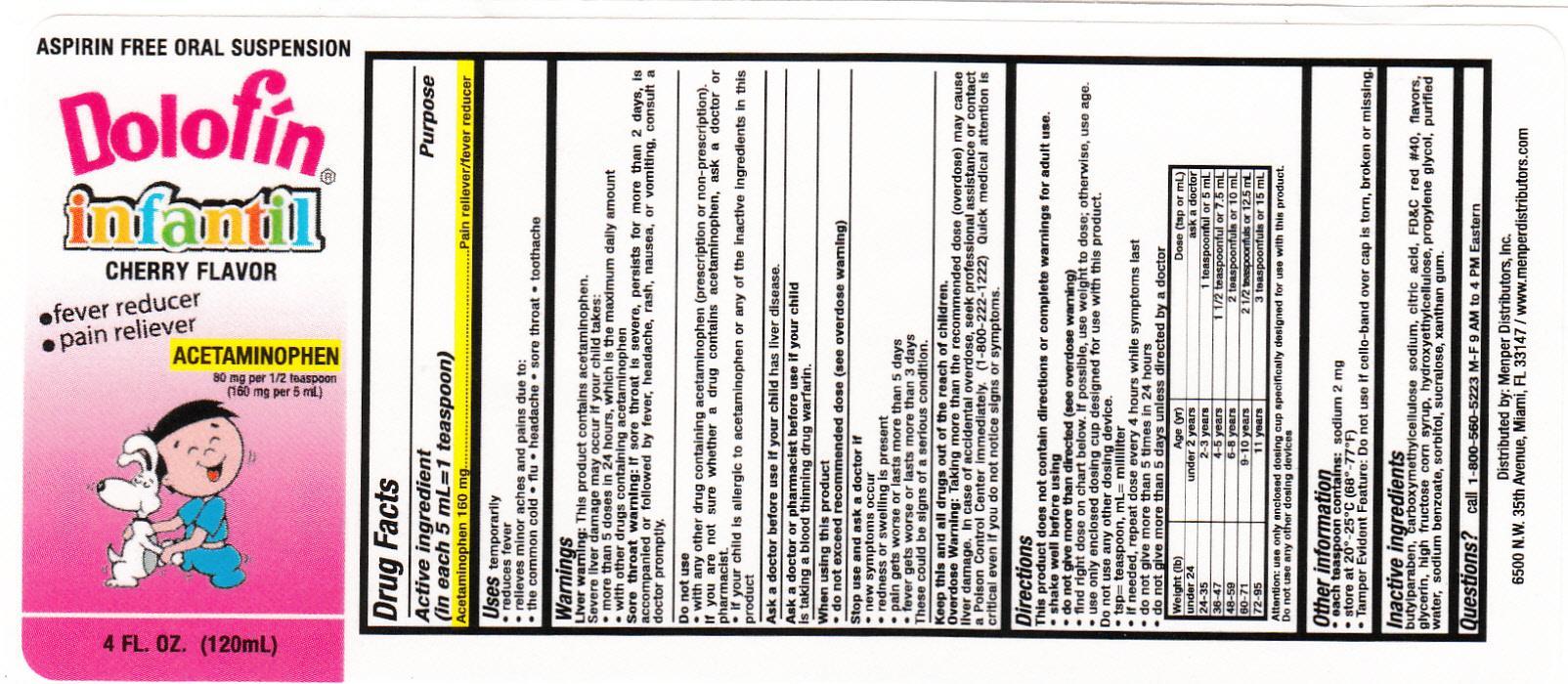 DRUG LABEL: Dolofin Infantil
NDC: 53145-053 | Form: LIQUID
Manufacturer: Menper Distributors, Inc.
Category: otc | Type: HUMAN OTC DRUG LABEL
Date: 20130912

ACTIVE INGREDIENTS: ACETAMINOPHEN 160 mg/5 mL
INACTIVE INGREDIENTS: BUTYLPARABEN; CARBOXYMETHYLCELLULOSE SODIUM; CITRIC ACID ACETATE; FD&C RED NO. 40; GLYCERIN; HIGH FRUCTOSE CORN SYRUP; HYDROXYETHYL CELLULOSE (100 MPA.S AT 2%); PROPYLENE GLYCOL; WATER; SODIUM BENZOATE; SORBITOL; SUCRALOSE; XANTHAN GUM

Active Ingredient

Acetaminophen 160 mg

Purpose

Acetaminophen.............................Pain reliever/fever reducer

Uses

temporarily reduces fever
temporarily relieves minor aches and pains due to:
• the common cold • flu • headache
• sore throat • toothache

Warnings

Liver warning: This product contains acetaminophen.
Severe liver damage may occur if your child takes:
• more than 5 doses in 24 hours, which is the
maximum daily amount
• with other drugs containing acetaminophen
Sore throat warning: If sore throat is severe, persists for more than 2 days, is accompanied or followed by
fever, headache, rash, nausea, or vomiting, consult a
doctor promptly.

Ask a doctor before use if your child has

liver disease.

Ask a doctor or pharmacist before use if your child is

taking the blood thinning drug warfarin.

When using this product

• do not exceed recommended dose
(see overdose warning)

Stop use and ask a doctor if

• new symptoms occur
• redness or swelling is present
• pain gets worse or lasts more than 5 days
• fever gets worse or lasts more than 3 days
These could be signs of a serious condition.

KEEP OUT OF REACH OF CHILDREN

Keep this and all drugs out of the reach of children.

Overdose Warning: Taking more than the
recommended dose (overdose) may cause liver damage. In case of accidental overdose, seek
professional assistance or contact a Poison Control
Center immediately. Quick medical attention is
critical even if you do not notice any signs or
symptoms.

Directions

• this product does not contain directions or
complete warnings for adult use.
• shake well before using
• find right dose on chart below. If possible, use
weight to dose; otherwise, use age.
• use only enclosed dosing cup designed for use
with this product. Do not use any other dosing
device.
• if needed, repeat dose every 4 hours while
symptoms last
• do not give more than 5 times in 24 hours
• do not give more than 5 days unless directed
by a doctor

Weight (lb) Age (yr) Dose (tsp or mL)
under 24 under 2 ask a doctor
24-35 2-3 1 teaspoon or 5 mL
36-47 4-5 1 1/2 teaspoons or 7.5 mL
48-59 6-8 2 teaspoons or 10 mL
60-71 9-10 2 1/2 teaspoons or 12.5 mL
72-95 11 3 teaspoons or 15 mL

Other information

• store at controlled room temperature
• see bottom panel for lot number and
expiration date

Inactive Ingredients

acesulfame potassium, butyl paraben,
carboxymethylcellulose sodium, cellulose, citric acid,
flavors, glycerin, high fructose corn syrup, propylene
glycol, purified water, red 40, sodium benzoate,
sorbitol, xanthan gum